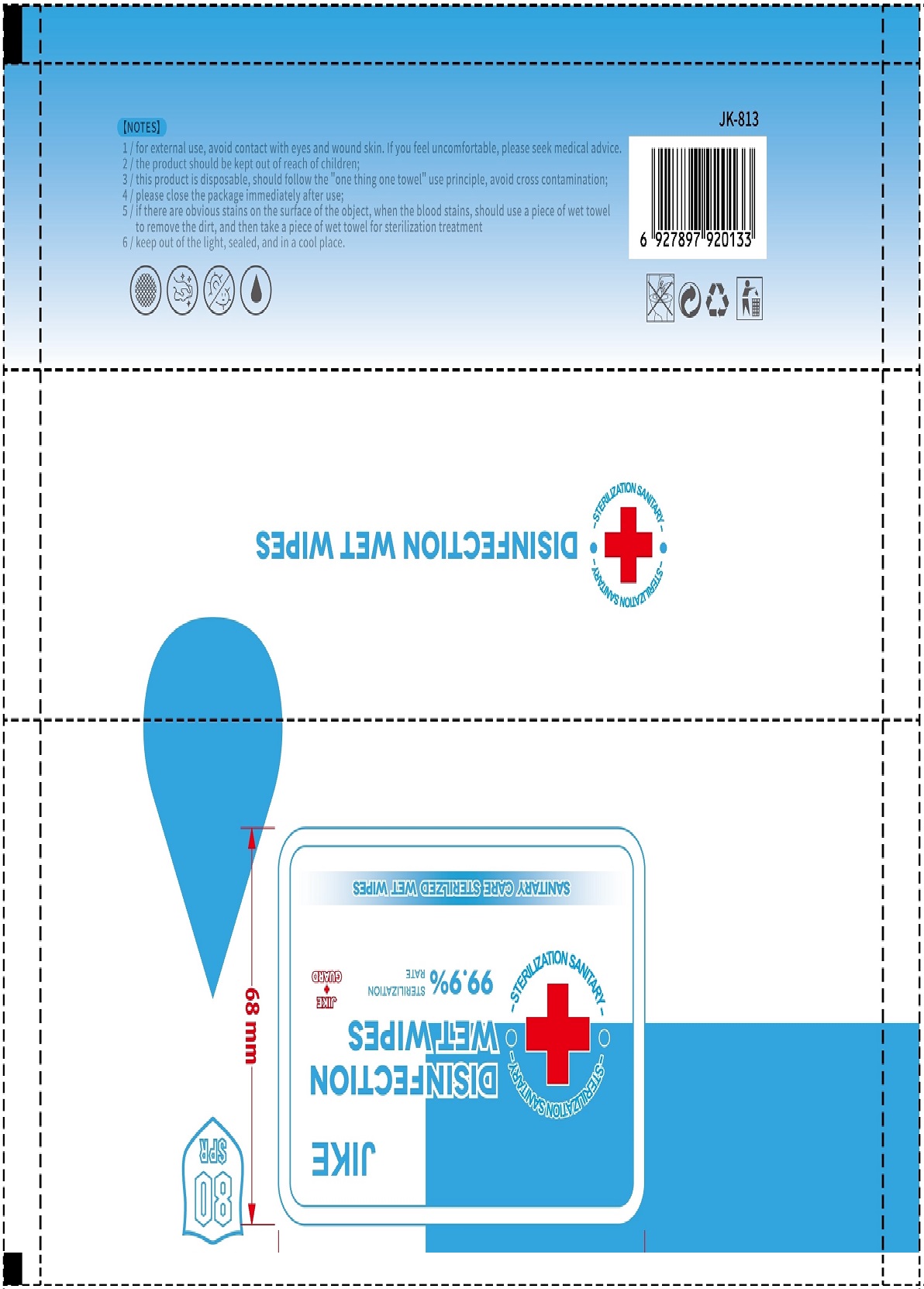 DRUG LABEL: Disinfection Wet Wipes
NDC: 42003-101 | Form: PATCH
Manufacturer: Zhejiang Jiayan Daily Commodity Co., Ltd
Category: otc | Type: HUMAN OTC DRUG LABEL
Date: 20200507

ACTIVE INGREDIENTS: BENZALKONIUM CHLORIDE 0.15 U/100 U; PHENOXYETHANOL 0.5 U/100 U
INACTIVE INGREDIENTS: GLYCERIN; DIDECYLDIMONIUM CHLORIDE; PROPYLENE GLYCOL; ETHYLHEXYLGLYCERIN; WATER

Jiayan, Disinfecting wet wipe, *80

Active ingredient

Phenoxyethanol, 0.5% w/w;

Benzalkonium Chloride, 0.15% w/w.

Inactive ingredient

Ethylhexylglycerin; Didecyldimonium Chloride; Propylene Glycol; Glycerin; Water.

Purpose

Kill the intestinal pathogenic bacterium, staphylococcus aureus pseudomonas aeruginosa candida albicans.

When using

Please close the pakage immediately after use.

If there are obvious stains on the surface of the object, when the blood stains, should use a piece of wet towel to remove the dirty, and then take a piece of wet towel for sterilization treatment.

Do not use

For external use, avoid contact with eyes and wound skin.

Stop use

If you feel uncomfortable, please seek medical advice.

Keep out of reach of children

The product should be kept out of reach of children.

Indications & usage

Applicable to the hand skin, object surface and medical equipment surface cleaning sterilization.

Dosage & administration

Open the package of wet towel and take out and unfold the wet towel.

From one side of the surface of the object, from the top down by the s-type wipe to the entire surface, action for 3 minutes.

Warnings

For external use, avoid contact with eyes and wound skin.

This product is disposable, should follow the "one thing one towel" use principle, avoid cross contamination.

Other information

Keep out of the light, sealed, and in a cool place.